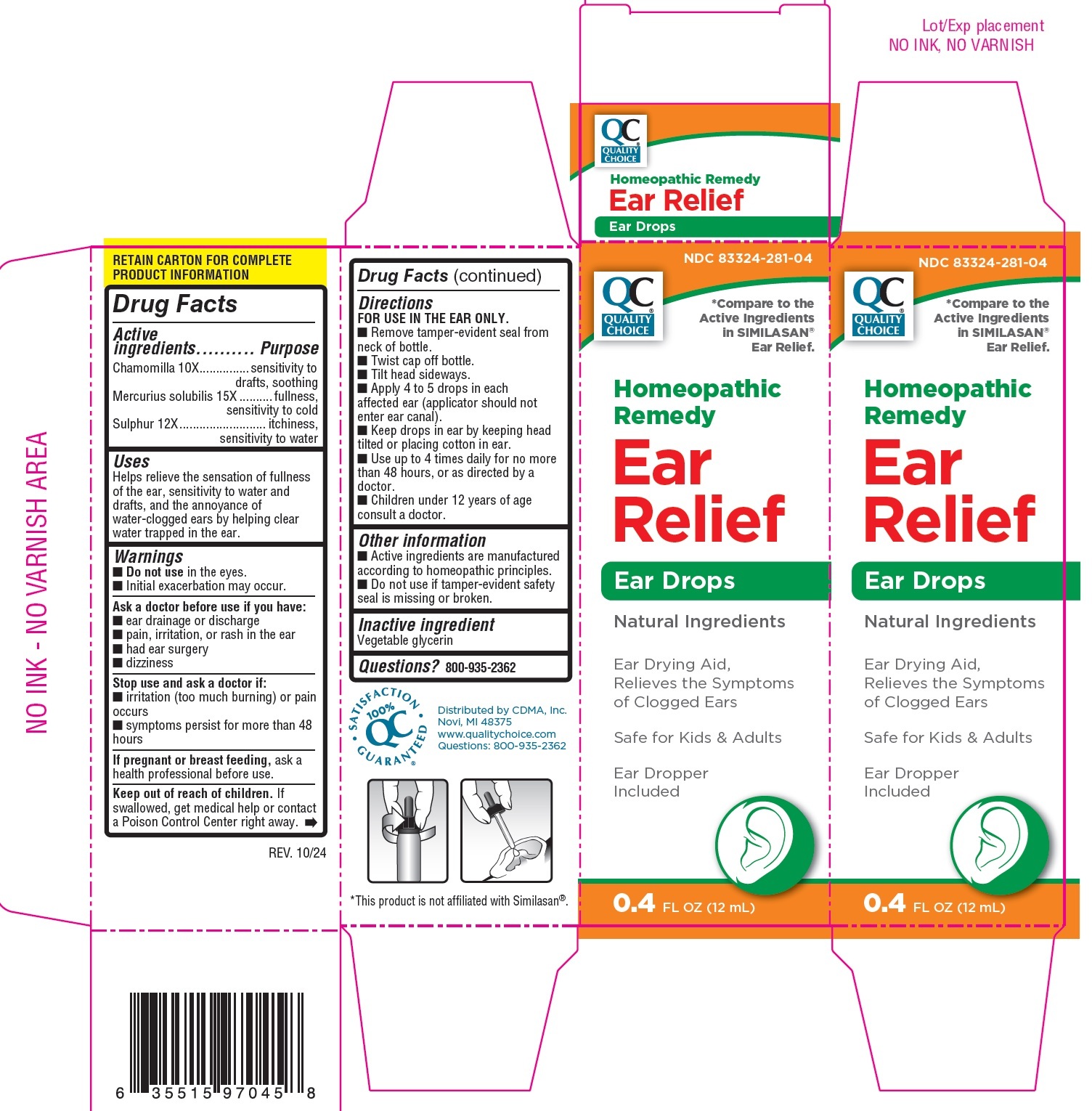 DRUG LABEL: QUALITY CHOICE Ear Relief Drops
NDC: 83324-281 | Form: SOLUTION
Manufacturer: Chain Drug Marketing Association, Inc
Category: homeopathic | Type: HUMAN OTC DRUG LABEL
Date: 20250228

ACTIVE INGREDIENTS: CHAMOMILE 10 [hp_X]/1 mL; MERCURIUS SOLUBILIS 15 [hp_X]/1 mL; SULFUR 12 [hp_X]/1 mL
INACTIVE INGREDIENTS: GLYCERIN

QUALITY CHOICE Ear Relief Drops

Active ingredients

Chamomilla 10X

Mercurius solubilis 15X

Sulphur 12X

Purpose

sensitivity to drafts, soothing

fullness, sensitivity to cold

itchiness, sensitivity to water

Uses

Helps relieve the sensation of fullness of the ear, sensitivity to water and drafts, and the annoyance of water-clogged ears by helping clear water trapped in the ear.

Warnings

Do not use

- in the eyes.
- Initial exacerbation may occur.

Ask a doctor before use if you have:

- ear drainage or discharge
- pain, irritation, or rash in the ear
- had ear surgery
- dizziness

Stop use and ask a doctor if:

- irritation (too much burning) or pain occurs
- symptoms persist for more than 48 hours

If pregnant or breast feeding,

ask a health professional before use.

Keep out of reach of children.

If swallowed, get medical help or contact a Poison Control Center right away.

Directions

FOR USE IN THE EAR ONLY.

- Remove tamper-evident seal from neck of bottle.
- Twist cap off bottle.
- Tilt head sideways.
- Apply 4 to 5 drops in each affected ear (applicator should not enter ear canal).
- Keep drops in ear by keeping head tilted or placing cotton in ear.
- Use up to 4 times daily for no more than 48 hours, or as directed by a doctor.
- Children under 12 years of age consult a doctor.

Other information

- Active ingredients are manufactured according to homeopathic principles.
- Do not use if tamper-evident safety seal is missing or broken.

Inactive ingredient

Vegetable glycerin

Questions?

800-935-2362